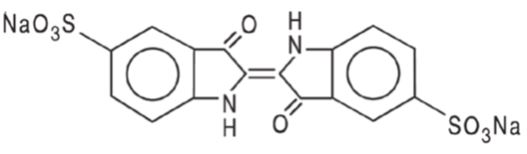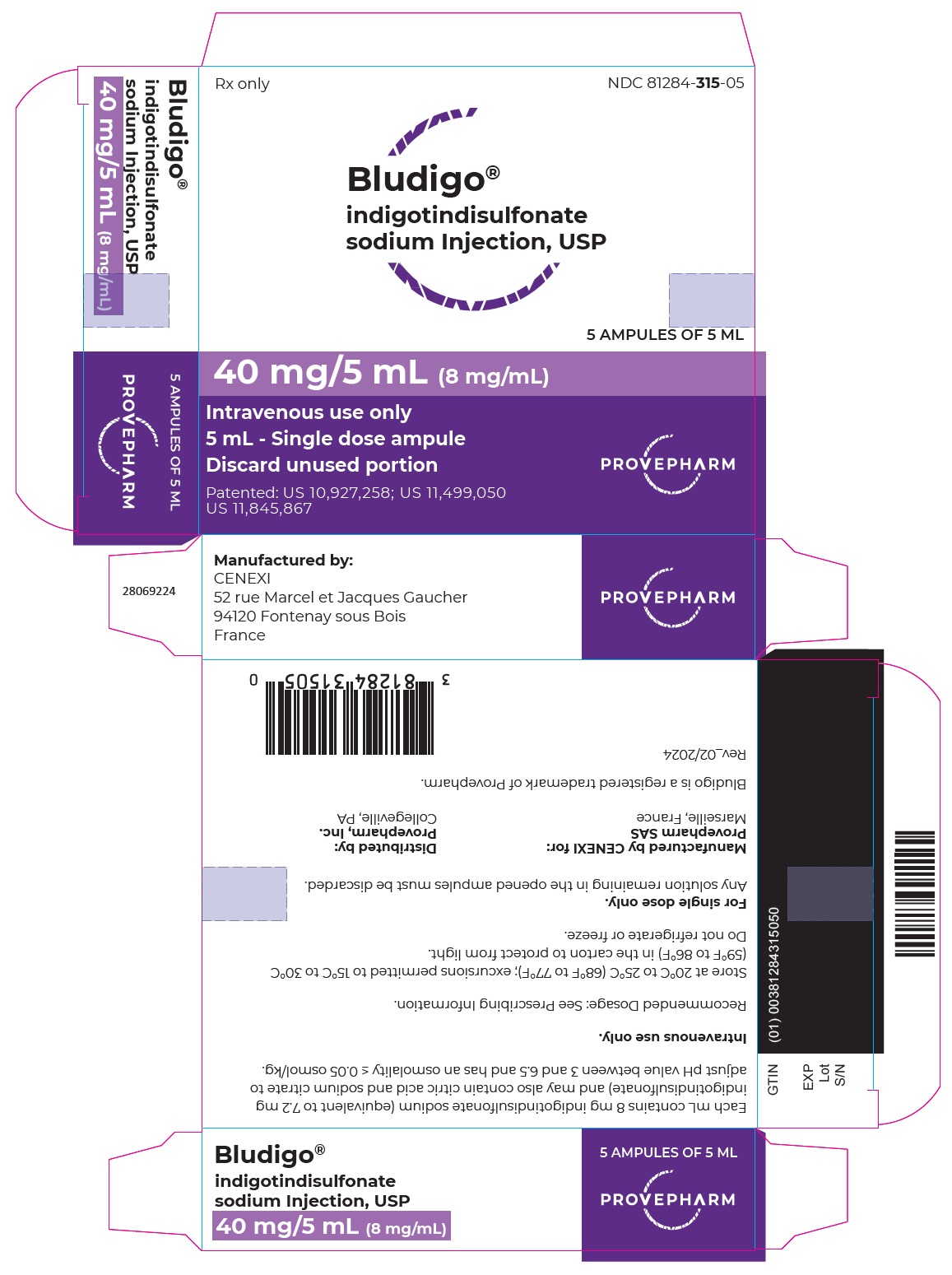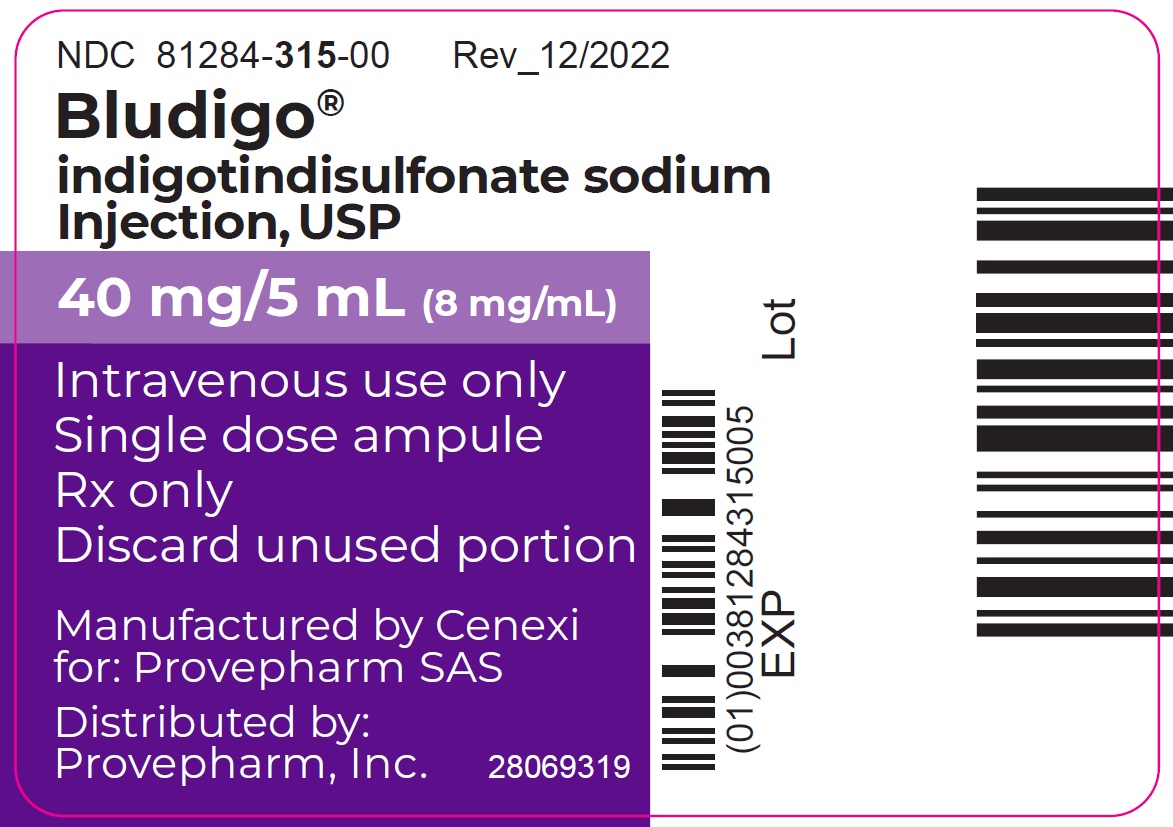 DRUG LABEL: BLUDIGO
NDC: 81284-315 | Form: INJECTION
Manufacturer: Provepharm Inc.
Category: prescription | Type: HUMAN PRESCRIPTION DRUG LABEL
Date: 20251111

ACTIVE INGREDIENTS: INDIGOTINDISULFONATE SODIUM 8 mg/1 mL
INACTIVE INGREDIENTS: CITRIC ACID MONOHYDRATE; SODIUM CITRATE

HIGHLIGHTS OF PRESCRIBING INFORMATION

These highlights do not include all the information needed to use BLUDIGO safely and effectively. See full prescribing information for BLUDIGO.
BLUDIGO® (indigotindisulfonate sodium injection), for
intravenous use
Initial U.S. Approval: 2022

1 INDICATIONS AND USAGE

BLUDIGO is a diagnostic dye indicated for use as a visualization aid in the cystoscopic assessment of the integrity of the ureters in adults following urological and gynecological open, robotic, or endoscopic surgical procedures. (1)

2 DOSAGE AND ADMINISTRATION

- Recommended dose is 5 mL given intravenously over 1 minute. (2.1)
- Monitor blood pressure and heart rhythm during and after injection. (2.2)

3 DOSAGE FORMS AND STRENGTHS

Injection: 40 mg/5 mL (8 mg/mL) indigotindisulfonate sodium in a single-dose ampule (3)

4 CONTRAINDICATIONS

- Known hypersensitivity to indigotindisulfonate or any of its components. (4)

5 WARNINGS AND PRECAUTIONS

- Cardiovascular Reactions: Severe or life-threatening cardiovascular reactions including cardiac arrest, arrhythmia, asystole, atrioventricular block second degree, hypotension, elevation in blood pressure, bradycardia, and tachycardia have been reported. Closely monitor blood pressure and cardiac rhythm during and following the BLUDIGO injection. Interrupt administration if reactions are observed. (5.1)
- Hypersensitivity Reactions: Serious anaphylactic reactions with hypotension, dyspnea, bronchospasm, urticaria, or erythema have been reported. Monitor patients for anaphylactic reactions and have emergency equipment and trained personnel readily available. (5.2)
- Interference with Oximetry Measurements:
  Anesthesiologists should be aware of the potential for artifactual reduction in SpO2 when anesthetized patients are administered BLUDIGO. (5.3)

6 ADVERSE REACTIONS

Adverse reactions (≥ 1%) are constipation, nausea, vomiting, abdominal pain, pyrexia, ALT increase, and dysuria. (6.1)

To report SUSPECTED ADVERSE REACTIONS, contact PROVEPHARM Inc at 1–833-727-6556 or FDA at 1-800-FDA-1088 or www.fda.gov/medwatch.

8 USE IN SPECIFIC POPULATIONS

- Renal Impairment: BLUDIGO is not recommended for use in patients with eGFR<30 mL/min. (8.6)

FULL PRESCRIBING INFORMATION

1 INDICATIONS AND USAGE

BLUDIGO is indicated for use as a visualization aid in the cystoscopic assessment of the integrity of the ureters in adults following urological and gynecological open, robotic, or endoscopic surgical procedures.

2 DOSAGE AND ADMINISTRATION

2.1 Recommended Dosage

The recommended dose of BLUDIGO is 5 mL given as an intravenous injection over 1 minute.
The blue color is detectable at the ureteral orifices within 4 minutes to 9 minutes after the intravenous injection.

2.2 Important Administration Instructions

- Monitor blood pressure and cardiac rhythm during and following the injection [see Warnings and Precautions (5.1)].
- Use immediately after opening ampule.
- Withdraw the contents of the ampule through a 5 micron or smaller filter straw/filter needle to ensure that the withdrawn solution contains no particulates. The withdrawn solution should be inspected visually for particulate matter and discoloration prior to administration.
- Do not administer with infusion assemblies used with other diluents or drugs.
- Discard any unused portion.

3 DOSAGE FORMS AND STRENGTHS

Injection: 40 mg/5 mL (8 mg/mL) indigotindisulfonate sodium as a dark blue or bluish-purple solution in a single-dose amber glass ampule.

4 CONTRAINDICATIONS

BLUDIGO is contraindicated in patients with known hypersensitivity to indigotindisulfonate or any of its components [see Warnings and Precautions (5.2)].

5 WARNINGS AND PRECAUTIONS

5.1 Cardiovascular Reactions

Severe or life-threatening cardiovascular reactions including cardiac arrest, arrhythmia, asystole, second degree atrioventricular block, hypotension, elevation in blood pressure, bradycardia, and tachycardia have been reported generally within 60 minutes following administration of indigotindisulfonate sodium injection products and required urgent intervention [see Adverse Reactions (6.2)].

Indigotindisulfonate may cause vasoconstriction by interference with vasodilation mediated by nitric oxide dependent mechanisms and by direct vasoconstriction. Indigotindisulfonate may also cause hypotension. Patients with hypertension, heart rate and conduction disorders, or medications causing bradycardia may be at increased risk for elevated blood pressure, hypotension, and bradycardia.

Closely monitor blood pressure and cardiac rhythm during and following the injection of BLUDIGO. Interrupt administration if reactions are observed.

5.2 Hypersensitivity Reactions

Serious anaphylactic reactions with hypotension, dyspnea, bronchospasm, urticaria, or erythema have been reported with the use of indigotindisulfonate sodium injection products [see Adverse Reactions (6.2)]. BLUDIGO is contraindicated in patients with known hypersensitivity to indigotindisulfonate [see Contraindications (4)]. Monitor patients for anaphylactic reactions and have emergency equipment and trained personnel readily available.

5.3 Interference with Oximetry Measurements

Indigotindisulfonate has been reported to interfere with light absorption and transiently interfere with pulse oximetric methods. Anesthesiologists should be aware of the potential for artifactual reduction in SpO2 when anesthetized patients are administered BLUDIGO.

6 ADVERSE REACTIONS

Clinically significant adverse reactions are described elsewhere in the labeling:

- Cardiovascular Reactions [see Warnings and Precautions (5.1)]
- Hypersensitivity Reactions [see Warnings and Precautions (5.2)]

6.1 Clinical Trials Experience

Because clinical trials are conducted under widely varying conditions, adverse reaction rates observed in the clinical trials of a drug cannot be directly compared to rates in the clinical trials of another drug and may not reflect the rates observed in practice. The safety of BLUDIGO was evaluated in a randomized, intra-patient controlled, blind to dose of BLUDIGO, clinical trial. A total of 118 adult patients undergoing endoscopic urological or gynecological procedures were treated intravenously; 58 (49%) of these patients received one dose of BLUDIGO 2.5 mL and 60 (51%) of patients received one dose of BLUDIGO 5 mL. The 2.5 mL dose is not approved [see Dosage and Administration (2.1)]. The mean age of patients was 51 years and 35 (30%) patients were 65 years of age or older. The majority of patients were White 105 (89%) and female 87 (74%).

The adverse reactions (≥1%) reported in the clinical trial are provided in Table 1.

Table 1. Adverse Reactions Reported at ≥1% of Patients Receiving BLUDIGO 5 mL Intravenously

 | BLUDIGO 5 mL (N=60) n (%)
Constipation | 3 (5.0)
Nausea | 2 (3.3)
Vomiting | 2 (3.3)
Abdominal Pain | 2 (3.3)
Pyrexia | 2 (3.3)
ALT increase | 2 (3.3)
Dysuria | 1 (1.7)

6.2 Postmarketing Experience

The following adverse reactions have been identified following the use of indigotindisulfonate sodium injection products.
Because these reactions are reported voluntarily from a population of uncertain size, it is not always possible to reliably estimate their frequency or establish a causal relationship to drug exposure.
Cardiovascular disorders: cardiac arrest, arrhythmia, asystole, atrioventricular block second degree, hypotension, elevation in blood pressure, bradycardia, tachycardia
General disorders and administration site conditions: injection site discoloration

Immune system disorders: anaphylactic reactions with hypotension, dyspnea, bronchospasm, urticaria, erythema

8 USE IN SPECIFIC POPULATIONS

8.1 Pregnancy

Risk Summary
Available data from case reports, case series, observational studies and clinical experience with indigotindisulfonate sodium injection use in pregnant women over several decades have not identified a drug associated risk of adverse maternal and fetal adverse effects. Indigotindisulfonate sodium injection use during the first trimester of pregnancy is rare; thus, the data are insufficient to evaluate for a drug associated risk of major birth defects and miscarriage. The majority of the published data were from intra-amniotic injections. Animal reproduction studies using the intravenous route of administration have not been conducted. Oral administration of indigotindisulfonate sodium to pregnant rats and rabbits produced no evidence of fetal harm.
However, oral availability is low (3%) so that the risk of intravenous administration of indigotindisulfonate sodium during pregnancy cannot be evaluated from the data available .
The estimated background risk of major birth defects and miscarriage for the indicated population is unknown. All pregnancies have a background risk of birth defects, loss, or other adverse outcomes. In the U.S. general population, the estimated background risk of major birth defects and miscarriage in clinically recognized pregnancies is 2 to 4% and 15 to 20%, respectively.

8.2 Lactation

Risk Summary
It is not known if indigotindisulfonate is present in animal or human milk. The transfer of indigotindisulfonate into breastmilk is likely to be low and adverse effects on the breastfed infant are not expected [see Clinical Pharmacology (12.3)]. There are no data on the effect of indigotindisulfonate on the breastfed infant or milk production. The developmental and health benefits of breastfeeding should be considered along with the mother’s clinical need for BLUDIGO and any potential adverse effects on the breastfed infant from BLUDIGO or from the underlying maternal condition.

8.4 Pediatric Use

The safety and effectiveness of BLUDIGO have not been established in pediatric patients.

8.5 Geriatric Use

Of the total number of subjects in the clinical study of BLUDIGO, 23 (20%) were 65 to 74 years of age, and 12 (10%) were 75 and older. No overall differences in safety or effectiveness were observed between these subjects and younger subjects, and other reported clinical experience has not identified differences in responses between the elderly and younger patients, but greater sensitivity of some older individuals cannot be ruled out.

8.6 Renal Impairment

Indigotindisulfonate is known to be excreted by the kidney through tubular secretion. No dedicated pharmacokinetic study using BLUDIGO in patients with varying degree of renal impairment has been conducted. Based on subgroup analyses in the randomized clinical trial, dose adjustment is not needed in patients with mild to moderate renal impairment (estimated glomerular filtration rate (eGFR) 30 to 89 mL/min derived from the Modification of Diet in Renal Disease formula).

BLUDIGO has not been studied in patients with eGFR < 30 mL/min and is not recommended for use in these patients.

11 DESCRIPTION

BLUDIGO (indigotindisulfonate sodium injection, USP) is a sterile deep blue or bluish-purple diagnostic dye for intravenous use.
Each mL contains 8 mg indigotindisulfonate sodium (equivalent to 7.2 mg indigotindisulfonate) and may also contain citric acid and sodium citrate to adjust pH value between 3 and 6.5 and has an osmolality ≤ 0.05 osmol/kg. Indigotindisulfonate sodium is also known as indigo carmine.
The chemical name of indigotindisulfonate sodium is Disodium 3,3’-dioxo-[Δ2,2’-biindoline]-5,5’-disulfonate. Its molecular formula is C16H8N2Na2O8S2 and its molecular weight is 466.35 g/mol. Its structural formula is:

indigotindisulfonate sodium

12 CLINICAL PHARMACOLOGY

12.1 Mechanism of Action

Indigotindisulfonate is a dye excreted by the kidney through tubular secretion and enhances visualization of the ureteral orifices by its deep blue color.

12.2 Pharmacodynamics

The blue color is detectable at the ureteral orifices within 4 minutes to 9 minutes after the intravenous injection.

12.3 Pharmacokinetics

The pharmacokinetic properties of BLUDIGO are presented in Table 2.

Table 2. Pharmacokinetics of Indigotindisulfonate in Healthy Adults Following Intravenous Administration of
BLUDIGO 5 mL (40 mg)

 |  | BLUDIGO
 |  | 5 mL (40 mg)
General Information
Cmax (CV%), μg/mL |  | 6.33 (58.4)
AUC0-INF (CV%), μg·h/mL |  | 1.15 (36.4)
Distribution
Mean (CV%) Volume of Distribution, L |  | 10.7 (36.1)
Protein Binding, in vitro |  | About 90%
Elimination
Mean (CV%) Elimination Half-life, minutes |  | 12 (34.1)
Mean (CV%) Clearance, L/hour | Urinary | 7.08 (66.3)
Mean (CV%) Clearance, L/hour | Total | 40.2 (45.1)
Metabolism
Primary Metabolic Pathways |  | Oxidative metabolism
Excretion
Urine (CV%)a |  | 16.0% (44.0)
Feces |  | <2%
aUnchanged drug
Cmax= maximum plasma concentration; AUC0-INF=area under the plasma concentration-time curve from time of administration extrapolated to infinity; CV=coefficient of variation

13 NONCLINICAL TOXICOLOGY

13.1 Carcinogenesis, Mutagenesis, Impairment of Fertility

Carcinogenicity
Carcinogenicity studies in animals have not been conducted with indigotindisulfonate sodium using the intravenous route of administration.
Long-term studies in mice with oral and subcutaneous administration of indigotindisulfonate sodium revealed no carcinogenic effects.

Mutagenesis
Although indigotindisulfonate sodium has been evaluated in a number of Ames assay studies, an Ames assay study that follows all currently recommended guidelines has not been performed. Indigotindisulfonate was not genotoxic in all those Ames assays.
The mutagenicity of indigotindisulfonate was inconclusive in the in vitro mouse L5187Y Lymphoma TK +/- assay. Orally administered indigotindisulfonate was not mutagenic in the in vivo mouse micronucleus test. An in vivo micronucleus test with indigotindisulfonate sodium using the intravenous route of administration has not been conducted.

Fertility
Fertility studies with indigotindisulfonate sodium using the intravenous route of administration have not been conducted.

14 CLINICAL STUDIES

The safety and efficacy of BLUDIGO were evaluated in a randomized intra-patient controlled, blind to dose of BLUDIGO, multi-center study (NCT04228445) in 118 adult patients undergoing endoscopic urological or gynecological surgical procedures including cystoscopic (58%), robotic (28%), and transvaginal (14%) approaches.

The majority of patients were white (89%), female (74%), and younger than 65 years of age (70%). Mean age was 51 years, and age ranged from 20 to 88 years.

Patients were randomized in a 1:1 ratio to receive 2.5 mL or 5 mL of BLUDIGO intravenously prior to the end of the surgical procedure. Each patient underwent cystoscopy and received 5 mL of sodium chloride injection 0.9% followed by the randomized BLUDIGO dose for visualization of urinary flow from the ureteral orifices. The 2.5 mL dose is not approved [see Dosage and Administration (2.1)].

The ureteral orifices and urine flow were observed and video recorded from 0 to 10 minutes post injection, with separate recordings made following sodium chloride injection and BLUDIGO. The conspicuity of the urine flow from the ureteral orifices was assessed in a randomized, blinded fashion by two independent central reviewers using a 5-point scale (1 = no urine flow observed; 2 = weak urine flow, little color contrast; 3 = Color contrast or significant urine flow; 4 = strong urine flow with good color contrast; and 5 = strong urine flow with striking contrast in color) once after sodium chloride injection and twice after BLUDIGO resulting in paired data. The surgeons also reviewed and scored conspicuity of the urine flow from the ureteral orifices. The responder for a ureter is defined as the difference in conspicuity score between BLUDIGO and sodium chloride injection being at least one point difference and the conspicuity score following BLUDIGO alone being greater than or equal to three. The reviewer agreement with the responder endpoint is acceptable. The proportion of responders along with its 95% confidence interval by ureter and reviewer or surgeon is summarized in Table 3.

Table 3. Summary of Proportion of Responders by Ureter and Reviewer or Surgeon in Patients Receiving BLUDIGO 5 mL

 | BLUDIGO 5 mL
 | Left Ureter (n=49) | Right Ureter (n=49)
Reviewer 1; % Responder*; 95% CL** | 63%; (48%, 77%) | 76%; (61%, 87%)
Reviewer 2; % responder; 95% CL | 78%; (63%, 88%) | 82%; (68%, 91%)
Surgeon; % responder; 95% CL | 71%; (57%, 83%) | 82%; (68%, 91%)

*responder: IC conspicuity score ≥ 3 and difference (IC – Saline) in conspicuity score ≥1, missing data is imputed as non-responder

** two-sided 95% confidence limits for the proportion of responder, calculated using the Clopper-Pearson (Exact) method

16 HOW SUPPLIED/STORAGE AND HANDLING

How Supplied
BLUDIGO (indigotindisulfonate sodium injection, USP) 40 mg/5 mL (8 mg/mL) is a dark blue or bluish-purple solution supplied in a carton of 5 single-dose amber glass ampules (NDC 81284-315-05).
Storage and Handling
Store at 20°C to 25°C (68°F to 77°F); excursions permitted to 15°C to 30°C (59° to 86°F) [See USP Controlled Room Temperature].
Store in original carton to protect from light.
Do not refrigerate or freeze.
Use immediately after opening ampule. Discard unused portion.

17 PATIENT COUNSELING INFORMATION

Cardiovascular Reactions
Advise the patient of the possibility of developing elevated blood pressure, hypotension, bradycardia, tachycardia, or atrioventricular block during or after the administration of BLUDIGO [see Warnings and Precautions (5.1)].

Injection Site and Urine Discoloration
Inform the patient that BLUDIGO may cause a blue discoloration of injection site and urine and that the discoloration should resolve within 48 hours. Advise the patient to inform the healthcare provider if the discoloration of the injection site is associated with other symptoms [see Adverse Reactions (6.2)].

Manufactured for:

PROVEPHARM SAS

13013 Marseille, FRANCE

Manufactured by:

CENEXI

52 rue Marcel et Jacques Gaucher

94120 Fontenay sous Bois, FRANCE

Distributed by:

PROVEPHARM INC.

Collegeville, PA 19426, USA

PRINCIPAL DISPLAY PANEL - CARTON

Rx only NDC 81284-315-05

Bludigo®
indigotindisulfonate
sodium Injection, USP

5 AMPULES OF 5 ML

40 mg/5 mL (8 mg/mL)

Intravenous use only
5 mL - Single dose ampule

Discard unused portion

Patented: US 10,927,258; US 11,499,050
US 11,845,867

PROVEPHARM

PRINCIPAL DISPLAY PANEL - VIAL

NDC 81284-315-00 Rev_12/2022

Bludigo®
indigotindisulfonate sodium
Injection, USP

40 mg/5 mL (8 mg/mL)

Intravenous use only

Single dose ampule

Rx only

Discard unused portion

Manufactured by Cenexi
for: Provepharm SAS

Distributed by:
Provepharm, Inc.

28069319